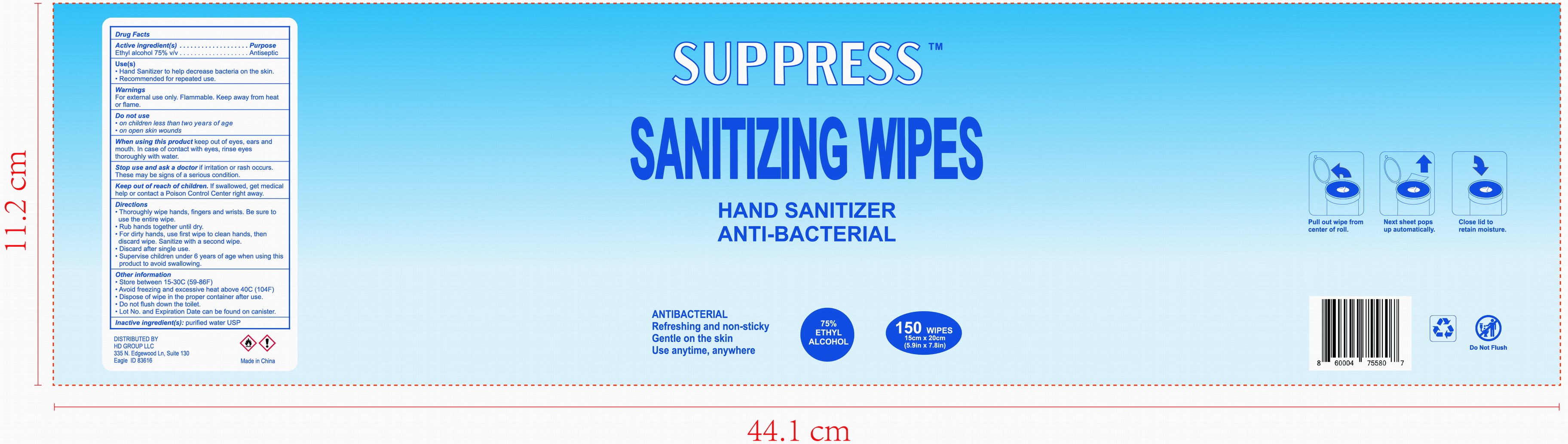 DRUG LABEL: SUPPRESS SANITIZIZING WIPES
NDC: 78183-011 | Form: CLOTH
Manufacturer: Kunming Ansheng Industry & Trade Co., Ltd.
Category: otc | Type: HUMAN OTC DRUG LABEL
Date: 20200916

ACTIVE INGREDIENTS: ALCOHOL 0.75 U/1 U
INACTIVE INGREDIENTS: WATER

SUPPRESS SANITIZIZING WIPES

Active Ingredient(s)

Ethyl acohol 75.0% v/v.

Purpose

To reduce bacteria on the skin and help prevent cross contamination.

Use

- Hand sanitizer to help reduce bacteria on the skin.
- Recommended for repeated use.

Warnings

For external use only. Flammable. Keep away from heat or flame

Do not use

- on children less than 2 months of age.
- on open skin wounds

When using this product keep out of eyes, ears and mouth. In case of contact with eyes, rinse eyes thoroughly with water.

Stop use and ask a doctor if irritation or rash occurs. These may be signs of a serious condition.

Keep out of reach of children. If swallowed, get medical help or contact a Poison Control Center right away.

Directions

- Rhoroughly wipe hands, fingers and wrists. Be sure to use the entire wipe.
- Rub hands together until dry.
- For dirty hands, use first wipe to clean hands, then discard wipe. Sanitize with a second wipe.
- Discard after single use.
- Supervise children under 6 years of age when using this product to avoid swallowing.

Inactive ingredients

Pure water USP.

OTHER INFORMATION

- Store between 15-30℃ (59-86℉)
- Avoid freezing and excessive heat about 40℃ (104℉)
- Dispose of wipe in the proper container after use.
- Do not flush down the toilet.
- Lot No. and Expiration date can be found on canister.

Package Label - Principal Display Panel

150 wipes in 1 canister.

NDC: 78183-011-01;